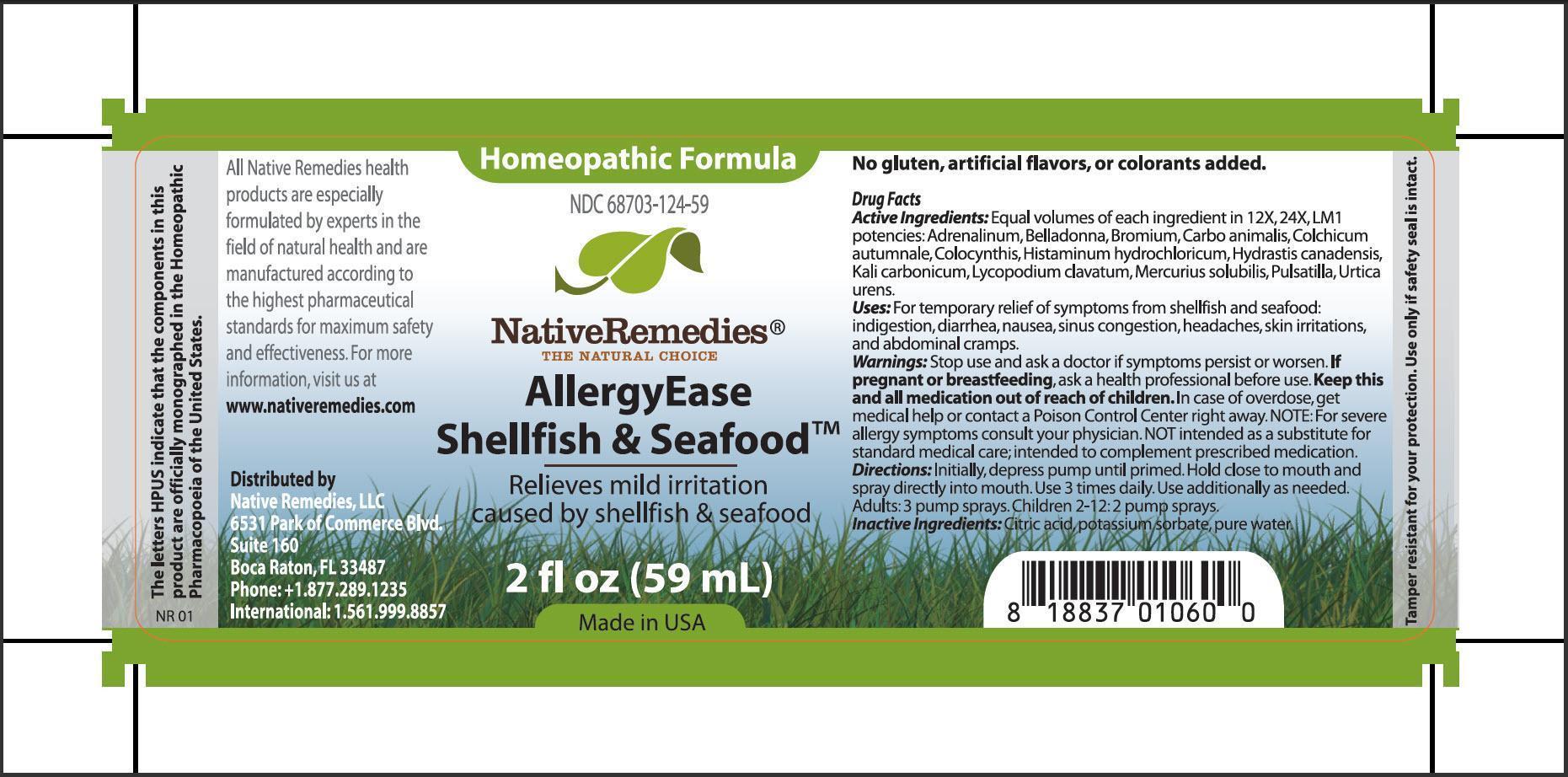 DRUG LABEL: AllergyEase Shellfish and Seafood
NDC: 68703-124 | Form: SPRAY
Manufacturer: Native Remedies, LLC
Category: homeopathic | Type: HUMAN OTC DRUG LABEL
Date: 20130613

ACTIVE INGREDIENTS: EPINEPHRINE 12 [hp_X]/59 mL; ATROPA BELLADONNA 12 [hp_X]/59 mL; BROMINE 12 [hp_X]/59 mL; Carbo Animalis 12 [hp_X]/59 mL; COLCHICUM AUTUMNALE BULB 12 [hp_X]/59 mL; CITRULLUS COLOCYNTHIS FRUIT PULP 12 [hp_X]/59 mL; HISTAMINE DIHYDROCHLORIDE 12 [hp_X]/59 mL; GOLDENSEAL 12 [hp_X]/59 mL; POTASSIUM CARBONATE 12 [hp_X]/59 mL; LYCOPODIUM CLAVATUM SPORE 12 [hp_X]/59 mL; MERCURIUS SOLUBILIS 12 [hp_X]/59 mL; PULSATILLA VULGARIS 12 [hp_X]/59 mL; URTICA URENS 12 [hp_X]/59 mL
INACTIVE INGREDIENTS: CITRIC ACID MONOHYDRATE; POTASSIUM SORBATE; WATER

AllergyEase Shellfish and Seafood

PURPOSE

Relieves mild irritation caused by shellfish and seafood

Drug Facts
Active Ingredients: Adrenalinum, Belladona, Bromium, Carbo animalis, Colchicum autumnale, Colocynthis, Histaminum hydrochloricum, Hydrstis canadensis, Kali carbonicum, Lycopodium clavatum, Mercuris solubilis, Pulsatilla, Urtica urens

INDICATIONS AND USAGE

Uses: For temporary relief of symptoms from shellfish and seafood: indigestions, diarrhea, nausea, sinus congestion, headaches, skin irritations, and abdominal cramps

WARNINGS

Warnings: Stop use and ask a doctor if symptoms persist or worsen

PREGNANCY OR BREAST FEEDING

If pregnant or breastfeeding, ask a health professional before use

KEEP OUT OF REACH OF CHILDREN

Keep this and all medications out of reach of children

OVERDOSAGE

In case of overdose, get medical help or contact a Poison Control Center right away. NOTE: For severe allergy symptoms consult your physician. NOT intended as a substitute for standard medical care; intended to complement prescribed medication

DOSAGE AND ADMINISTRATION

Directions: Initially, depress pump until primed. Hold close to mouth and spray directly into mouth. Use 3 times daily. Use additionally as needed. Adults: 3 pumps sprays. Children 2-12:2 pump sprays

Inactive Ingredients: Citric acid, potassium sorbate, pure water

PATIENT COUNSELING INFORMATION

The letters HPUS indicate that the components in this product are officially monographed in the Homeopathic Pharmacopoeia of the United States

All Native Remedies health products are especially formulated by experts in the field of natural health and are manufactured according to the highest pharmaceutical standards for maximum safety and effectiveness. For more information, visit us at www.nativeremedies.com

Distributed by
Native Remedies, LLC
6531 Park of Commerce Blvd.
Suite 160
Boca Raton, FL 33487
Phone: +1.877.289.1235
International: 1.561.999.8857

No gluten, artificial flavors, or colorants added

STORAGE AND HANDLING

Tamper resistant for your protection. Use only if safety seal is intact